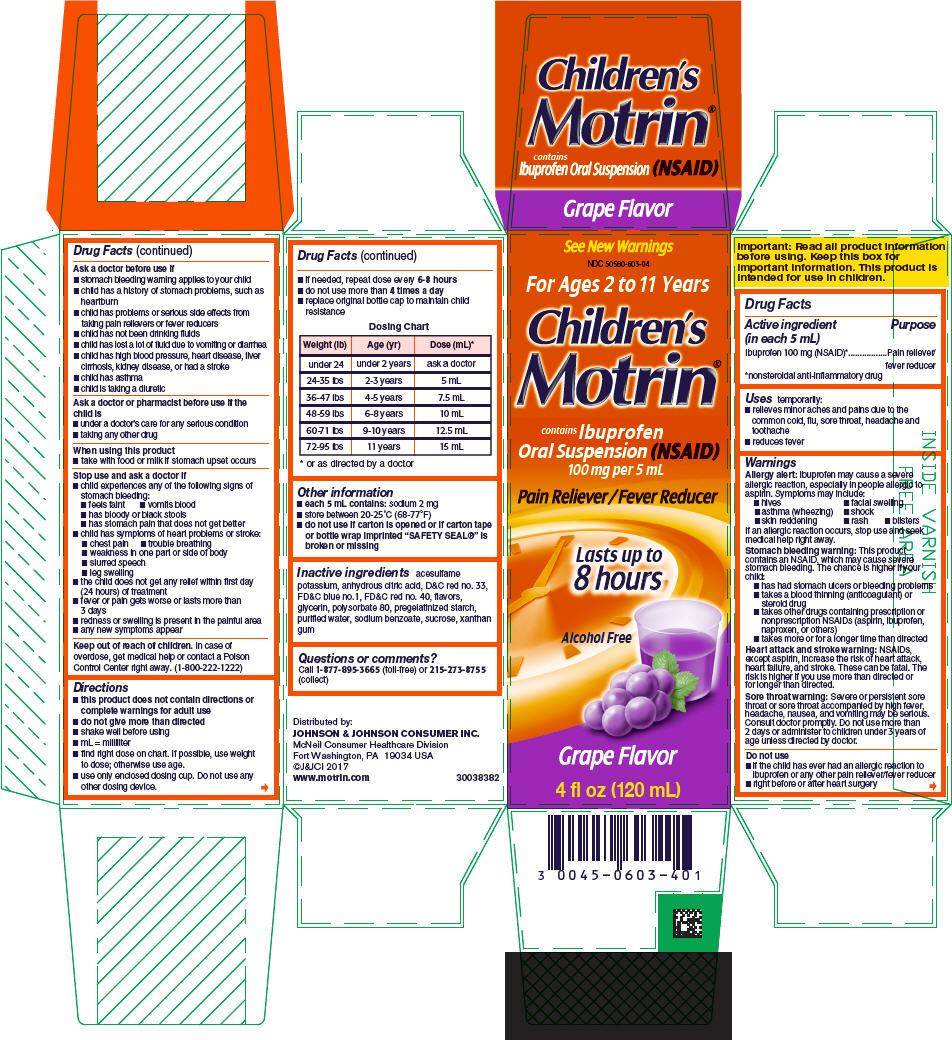 DRUG LABEL: Childrens Motrin
NDC: 50580-603 | Form: SUSPENSION
Manufacturer: Kenvue Brands LLC
Category: otc | Type: HUMAN OTC DRUG LABEL
Date: 20241108

ACTIVE INGREDIENTS: IBUPROFEN 100 mg/5 mL
INACTIVE INGREDIENTS: ACESULFAME POTASSIUM; ANHYDROUS CITRIC ACID; D&C RED NO. 33; FD&C BLUE NO. 1; FD&C RED NO. 40; GLYCERIN; POLYSORBATE 80; WATER; SODIUM BENZOATE; SUCROSE; XANTHAN GUM

Children's Motrin

Drug Facts

Active ingredient (in each 5 mL)

Ibuprofen 100 mg (NSAID) [nonsteroidal anti-inflammatory drug]

Purpose

Pain reliever/fever reducer

Uses

temporarily:

- relieves minor aches and pains due to the common cold, flu, sore throat, headache and toothache
- reduces fever

Warnings

Allergy alert

Ibuprofen may cause a severe allergic reaction, especially in people allergic to aspirin. Symptoms may include:

- hives
- facial swelling
- asthma (wheezing)
- shock
- skin reddening
- rash
- blisters

If an allergic reaction occurs, stop use and seek medical help right away.

Stomach bleeding warning

This product contains an NSAID, which may cause severe stomach bleeding. The chance is higher if your child:

- has had stomach ulcers or bleeding problems
- takes a blood thinning (anticoagulant) or steroid drug
- takes other drugs containing prescription or nonprescription NSAIDs (aspirin, ibuprofen, naproxen, or others)
- takes more or for a longer time than directed

Heart attack and stroke warning

NSAIDs, except aspirin, increase the risk of heart attack, heart failure, and stroke. These can be fatal. The risk is higher if you use more than directed or for longer than directed.

Sore throat warning

Severe or persistent sore throat or sore throat accompanied by high fever, headache, nausea, and vomiting may be serious. Consult doctor promptly. Do not use more than 2 days or administer to children under 3 years of age unless directed by doctor.

Do not use

- if the child has ever had an allergic reaction to ibuprofen or any other pain reliever/fever reducer
- right before or after heart surgery

Ask a doctor before use if

- stomach bleeding warning applies to your child
- child has a history of stomach problems, such as heartburn
- child has problems or serious side effects from taking pain relievers or fever reducers
- child has not been drinking fluids
- child has lost a lot of fluid due to vomiting or diarrhea
- child has high blood pressure, heart disease, liver cirrhosis, kidney disease, or had a stroke
- child has asthma
- child is taking a diuretic

Ask a doctor or pharmacist before use if the child is

- under a doctor's care for any serious condition
- taking any other drug

When using this product

- take with food or milk if stomach upset occurs

Stop use and ask a doctor if

- child experiences any of the following signs of stomach bleeding:
  - feels faint
  - vomits blood
  - has bloody or black stools
  - has stomach pain that does not get better
- child has symptoms of heart problems or stroke:
  - chest pain
  - trouble breathing
  - weakness in one part or side of body
  - slurred speech
  - leg swelling
- the child does not get any relief within first day (24 hours) of treatment
- fever or pain gets worse or lasts more than 3 days
- redness or swelling is present in the painful area
- any new symptoms appear

Keep out of reach of children. In case of overdose, get medical help or contact a Poison Control Center right away. (1-800-222-1222)

Directions

- this product does not contain directions or complete warnings for adult use
- do not give more than directed
- shake well before using
- mL = milliliter
- find right dose on chart. If possible, use weight to dose; otherwise use age.
- use only enclosed dosing cup. Do not use any other dosing device.
- if needed, repeat dose every 6-8 hours
- do not use more than 4 times a day
- replace original bottle cap to maintain child resistance

Dosing Chart
Weight (lb) | Age (yr) | Dose (mL) [or as directed by a doctor]
under 24 | under 2 years | ask a doctor
24-35 lbs | 2-3 years | 5 mL
36-47 lbs | 4-5 years | 7.5 mL
48-59 lbs | 6-8 years | 10 mL
60-71 lbs | 9-10 years | 12.5 mL
72-95 lbs | 11 years | 15 mL

Other information

- each 5 mL contains: sodium 2 mg
- store between 20-25°C (68-77°F)
- do not use if carton is opened or if carton tape or bottle wrap imprinted "SAFETY SEAL®" is broken or missing

Inactive ingredients

acesulfame potassium, anhydrous citric acid, D&C red no. 33, FD&C blue no.1, FD&C red no. 40, flavors, glycerin, polysorbate 80, pregelatinized starch, purified water, sodium benzoate, sucrose, xanthan gum

Questions or comments?

Call 1-877-895-3665 (toll-free) or 215-273-8755 (collect)

PRINCIPAL DISPLAY PANEL

See New Warnings

NDC 50580-603-04

For Ages 2 to 11 Years

Children's
Motrin®

contains Ibuprofen
Oral Suspension (NSAID)
100 mg per 5 mL

Pain Reliever / Fever Reducer

Lasts up to
8 hours

Alcohol Free

Grape Flavor

4 fl oz (120 mL)